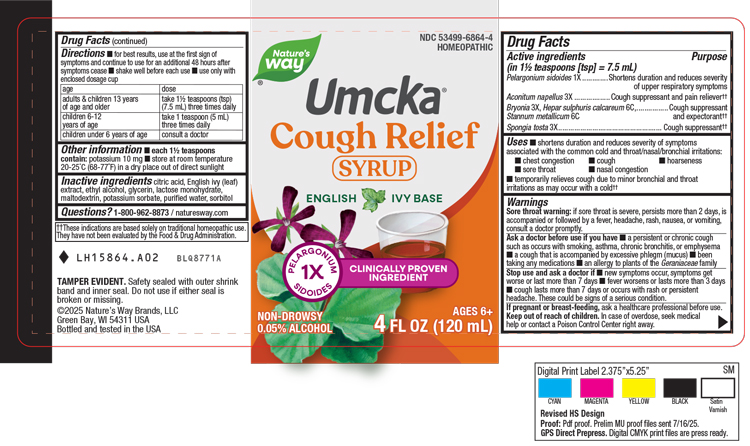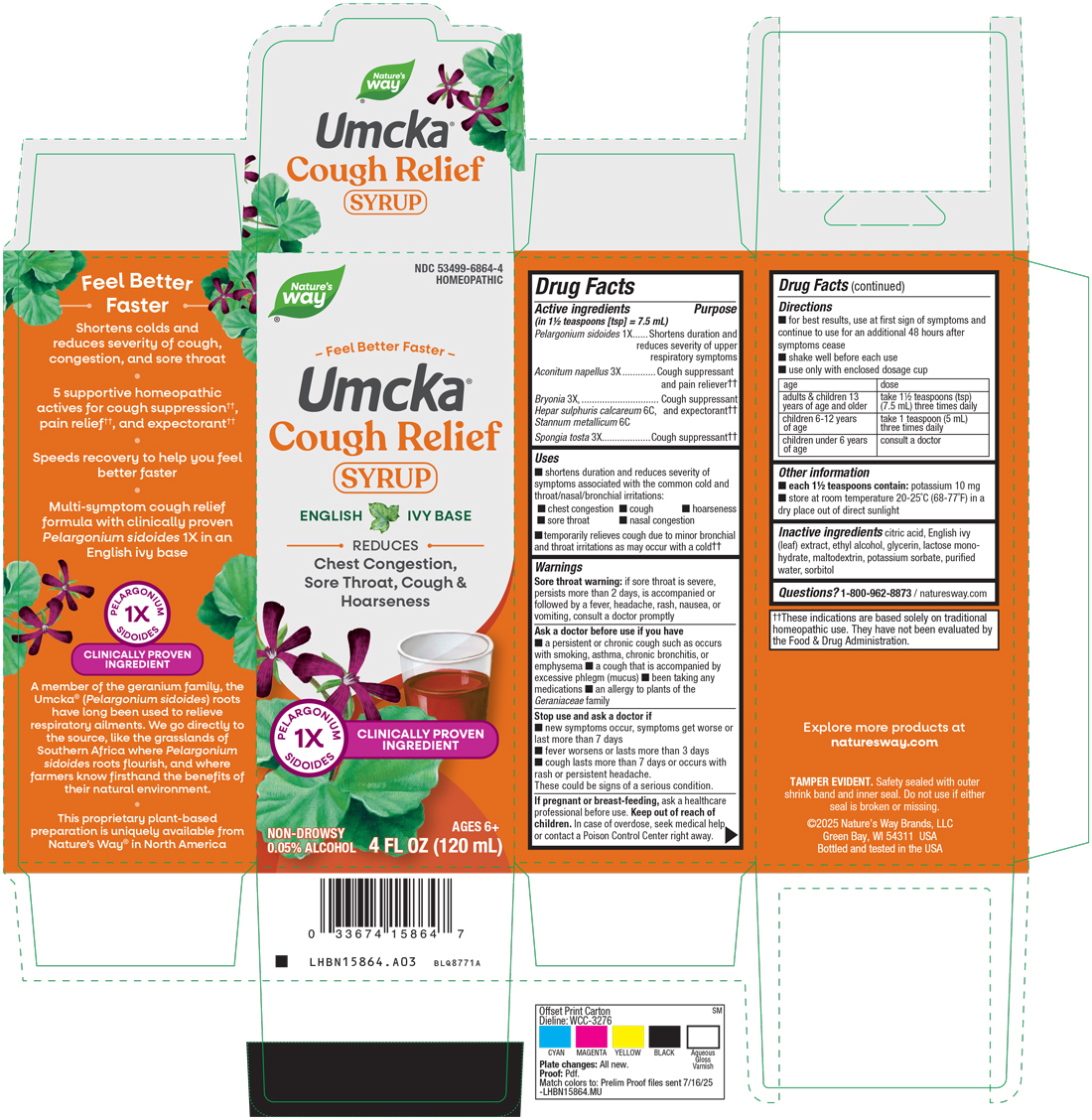 DRUG LABEL: Cough Relief
NDC: 53499-6864 | Form: SYRUP
Manufacturer: Schwabe North America, Inc.
Category: homeopathic | Type: HUMAN OTC DRUG LABEL
Date: 20250916

ACTIVE INGREDIENTS: PELARGONIUM SIDOIDES ROOT 1 [hp_X]/120 mL; ACONITUM NAPELLUS 3 [hp_X]/120 mL; BRYONIA ALBA ROOT 3 [hp_X]/120 mL; CALCIUM SULFIDE 6 [hp_C]/120 mL; TIN 6 [hp_C]/120 mL; SPONGIA OFFICINALIS SKELETON, ROASTED 3 [hp_X]/120 mL
INACTIVE INGREDIENTS: ANHYDROUS CITRIC ACID; HEDERA HELIX LEAF; ALCOHOL; GLYCERIN; LACTOSE MONOHYDRATE; MALTODEXTRIN; WATER; SORBITOL; POTASSIUM SORBATE

Cough Relief

Active Ingredients

Pelargonium sidoides 1X

Aconitum napellus 3X

Bryonia 3X

Hepar sulphuris calcareum 6C

Stannum metallicum 6C

Spongia tosta 3X

Inactive Ingredients

Citric Acid

English Ivy Leaf Extract

Ethyl Alcohol

Glycerin

Lactose Monohydrate

Maltodextrin

Potassium Sorbate

Purified Water

Sorbitol

Purpose

Shortens duration and reduces severity of symptoms associated with the common cold and throat/nasal/bronchial irritations: chest congestion, cough, hoarseness, sore throat, nasal congestion.

Temporarily relieves cough due to minor bronchial and throat irritations as may occur with a cold.

Indications & Usage

Shortens duration and reduces severity of symptoms associated with the common cold and throat/nasal/bronchial irritations: chest congestion, cough, hoarseness, sore throat, nasal congestion.

Temporarily relieves cough due to minor bronchial and throat irritations as may occur with a cold.

Doage & Administration

Directions

For best results, use at first sign of symptoms and continue to use for an additional 48 hours after symptoms cease.

Shake well before each use.

Use only with enclosed dosage cup.

Adults and Children 13 years of age and older: Take 1 ½ teaspoons (tsp) (7.5 mL) three times daily.

Children 6 to 12 years of age: Take 1 teaspoon (5 mL) three times daily.

Children under 6 years of age: Consult a doctor.

Warnings

Sore throat warning: if sore throat is severe, persists more than 2 days, is accompanied or followed by a fever, headache, rash, nausea, or vomiting, consult a doctor promptly.

Ask Doctor

Ask a doctor before use if you have a persistent or chronic cough such as occurs with smoking, asthma, chronic bronchitis or emphysema, a cough that is accompanied by excessive phlegm (mucus), been taking any medications, an allergy to plants of the Genaniaceae family.

Stop Use

Stop use and ask a doctor if new symptoms occur, symptoms get worse or last more than 7 days, fever worsens or lasts more than 3 days, cough lasts more than 7 days or occurs with rash or persistent headache.

These could be a sign of a serious condition.

Overdose

In case of overdose, seek medical help or contact a Poison Control Center right away.

Pregnancy or Breast Feeding

If pregnant or breast-feeding, ask a healthcare professional before use.

Keep out of reach of children